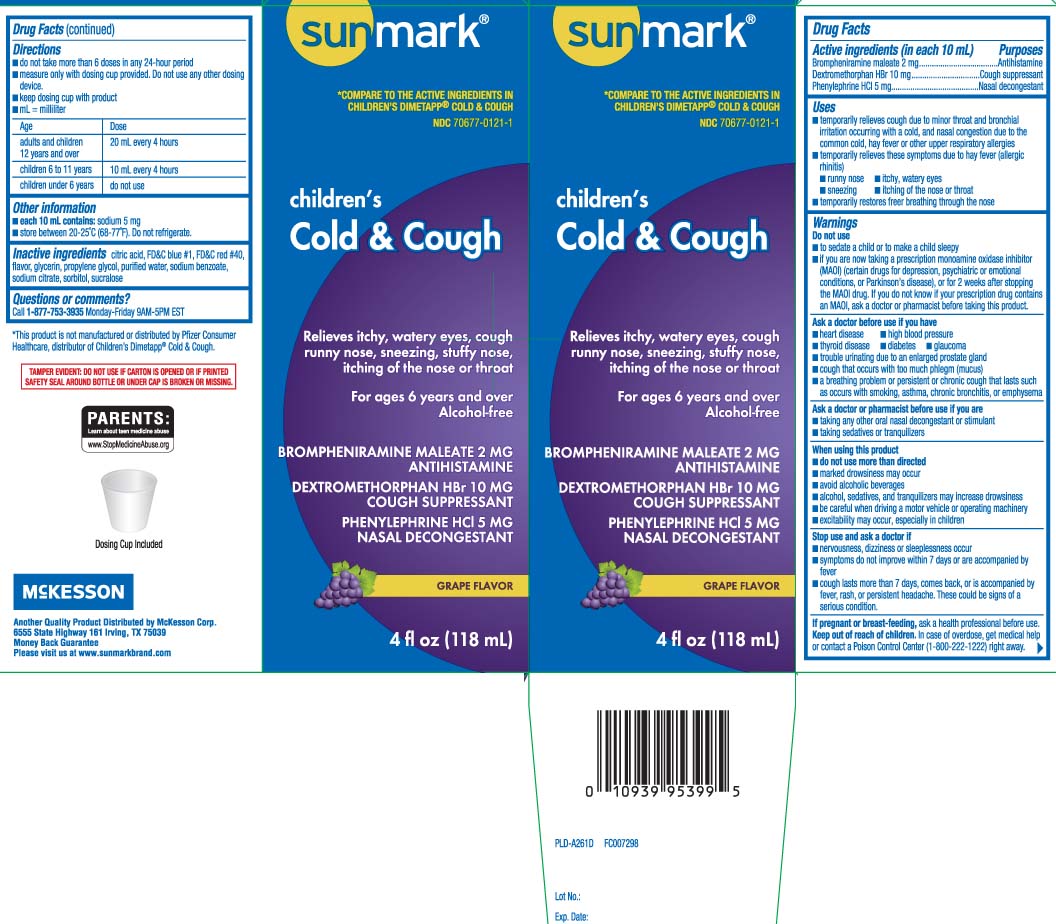 DRUG LABEL: Cold and Cough Relief
NDC: 70677-0121 | Form: LIQUID
Manufacturer: Strategic Sourcing Services LLC
Category: otc | Type: HUMAN OTC DRUG LABEL
Date: 20240530

ACTIVE INGREDIENTS: BROMPHENIRAMINE MALEATE 2 mg/10 mL; DEXTROMETHORPHAN HYDROBROMIDE 10 mg/10 mL; PHENYLEPHRINE HYDROCHLORIDE 5 mg/10 mL
INACTIVE INGREDIENTS: ANHYDROUS CITRIC ACID; FD&C BLUE NO. 1; FD&C RED NO. 40; GLYCERIN; PROPYLENE GLYCOL; WATER; SODIUM BENZOATE; TRISODIUM CITRATE DIHYDRATE; SORBITOL; SUCRALOSE

Drug Facts

Active ingredients (in each 10 mL)

Brompheniramine maleate 2 mg

Dextromethorphan HBr 10 mg

Phenylephrine HCl 5 mg

Purposes

Antihistamine

Cough suppressant

Nasal decongestant

Uses

- temporarily relieves cough due to minor throat and bronchial irritation occurring with a cold, and nasal congestion due to the common cold, hay fever or other upper respiratory allergies
- temporarily relieves these symptoms due to hay fever (allergic rhinitis):
  - runny nose
  - sneezing
  - itchy, watery eyes
  - itching of the nose or throat
- temporarily restores freer breathing through the nose

Warnings

Do not use

- to sedate a child or to make a child sleepy
- if you are now taking a prescription monoamine oxidase inhibitor (MAOI) (certain drugs for depression, psychiatric or emotional conditions, or Parkinson's disease), or for 2 weeks after stopping the MAOI drug. If you do not know if your prescription drug contains an MAOI, ask a doctor or pharmacist before taking this product.

Ask a doctor before use if you have

- heart disease
- high blood pressure
- thyroid disease
- diabetes
- glaucoma
- trouble urinating due to an enlarged prostate gland
- cough that occurs with too much phlegm (mucus)
- a breathing problem or persistent or chronic cough that lasts such occurs with smoking, asthma, chronic bronchitis, or emphysema

Ask a doctor or pharmacist before use if you are

- taking any other oral nasal decongestant or stimulant
- taking sedatives or tranquilizers

When using this product

- do not use more than directed
- marked drowsiness may occur
- avoid alcoholic beverages
- alcohol, sedatives, and tranquilizers may increase drowsiness
- be careful when driving a motor vehicle or operating machinery
- excitability may occur, especially in children

Stop use and ask a doctor if

- nervousness, dizziness or sleeplessness occurs
- symptoms do not improve within 7 days or are accompanied by fever
- cough lasts more than 7 days, comes back, or is accompanied by fever, rash, or persistent headache. These could be signs of a serious condition.

If pregnant or breast-feeding,

ask a health professional before use.

Keep out of reach of children.

In case of overdose, get medical help or contact a Poison Control Center (1-800-222-1222) right away.

Directions

- do not take more than 6 doses in a 24-hour period
- measure only with dosing cup provided. Do not use any other dosing device
- keep dosing cup with product
- mL = milliliter

age | dose
adults and children 12 years and over | 20 mL every 4 hours
children 6 to 11 years | 10 mL every 4 hours
children under 6 years | do not use

Other information

- each 10 mL contains: sodium 5 mg
- store between 20-25ºC (68-77ºF). Do not refrigerate

Inactive ingredients

citric acid, FD&C blue #1, FD&C red 40, flavor, glycerin, propylene glycol, purified water, sodium benzoate, sodium citrate, sorbitol, sucralose

Questions or comments?

Call 1-877-753-3935 Monday-Friday 9AM-5PM EST

Principal Display Panel

COMPARE TO THE ACTIVE INGREDIENTS IN CHILDREN'S DIMETAPP® COLD & COUGH

Children's

Cold & Cough Relief

Relieves itchy, watery eyes, cough, runny nose, sneezing, stuffy nose, itching of the nose or throat

For ages 6 years and over

Alcohol-free

BROMPHENIRAMINE MALEATE 2 MG

ANTIHISTAMINE

DEXTROMETHORPHAN HBr 10 MG

COUGH SUPPRESSANT

PHENYLEPHRINE HCl 5 MG

NASAL DECONGESTANT

GRAPE FLAVOR

fl oz (mL)

Dosing Cup Included

*This product is not manufactured or distributed by Pfizer Consumer Healthcare, distributor of Children's Dimetapp® Cold & Cough.

TAMPER EVIDENT: DO NOT USE IF CARTON IS OPENED OR IF PRINTED SAFETY SEAL AROUND BOTTLE OR UNDER CAP IS BROKEN OR MISSING.

Distributed by McKesson Corp.

6555 State Highway 161 Irving, TX 75039

www.sunmarkbrand.com

Package Label

SUNMARK Children's Cold & Cough Grape Flavor